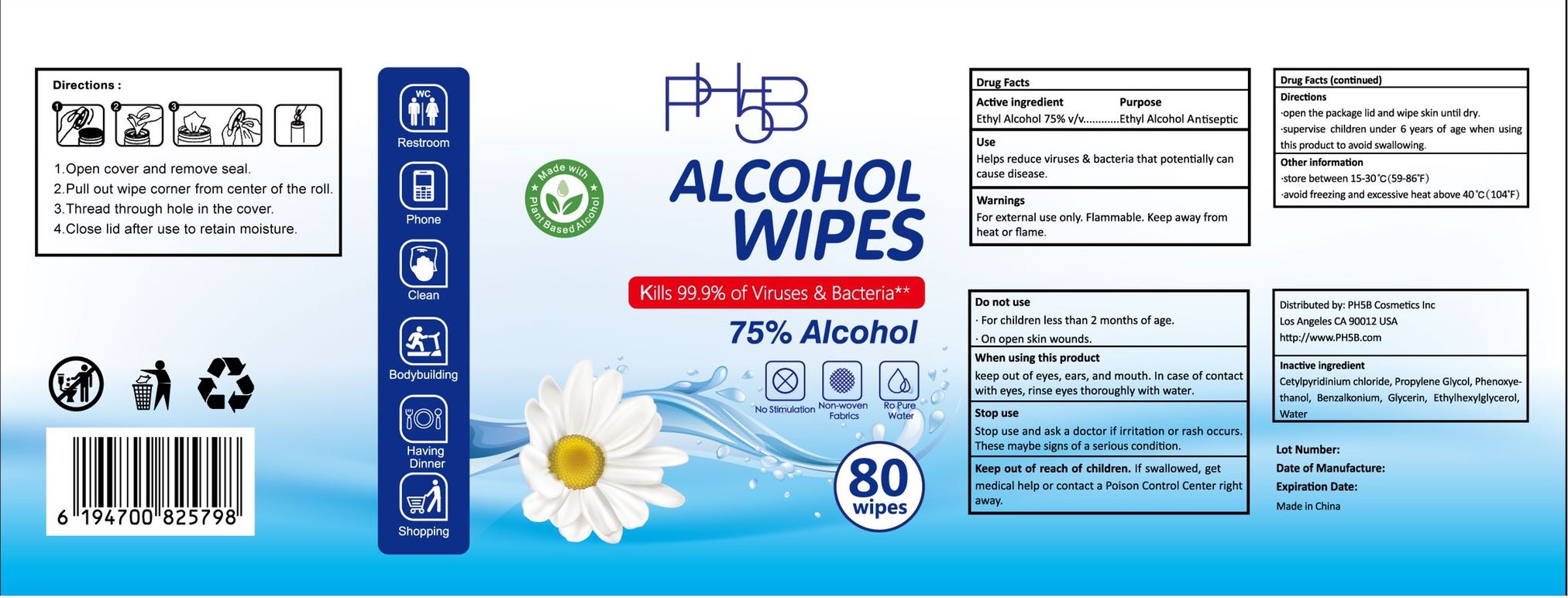 DRUG LABEL: PH5B Alcohol Wipes
NDC: 76718-009 | Form: SWAB
Manufacturer: Guangzhou Jukang Sanitary Products Co., Ltd.
Category: otc | Type: HUMAN OTC DRUG LABEL
Date: 20200811

ACTIVE INGREDIENTS: ALCOHOL 75 g/100 g
INACTIVE INGREDIENTS: WATER; CETYLPYRIDINIUM CHLORIDE; PROPYLENE GLYCOL; PHENOXYETHANOL; BENZALKONIUM; GLYCERIN

Wipes

Active Ingredient

Ethanol Alcohol 75%

Purpose

Antiseptic

USE

Helps reduce viruses and bacteria that potentially can caue disease.

Warning

Flammable, keep away from heat or flame.

For external use only.

Do not use

- For children less than 2 months of age
- On open skin wounds.

When using this product

Keep out of eyes, ears, and mouth. In case of contact with eyes, rinse eyes thoroughly with water.

Stop use

Stop use and ask a doctor if irritation or rash occurs. These maybe signs of a serious condition.

KEEP OUT OF REACH OF CHILDREN

If swallowed, get medical help or contact a Poison Contrl Center immediately.

Directions

- Open the package lid and wipe skin until dry.
- supervise children under 6 years of age when using this product to avoid swallowing.

Other information:

- store between 15-30℃ (59-86℉)
- avoid freezing and excessive heat above 40℃ (104℉)

Inactive ingredients

Cetylpyridinium chloride, propylene glycol, phenoxyethanol, benzalkonium, glycerin, ethylhexylglycerol, water